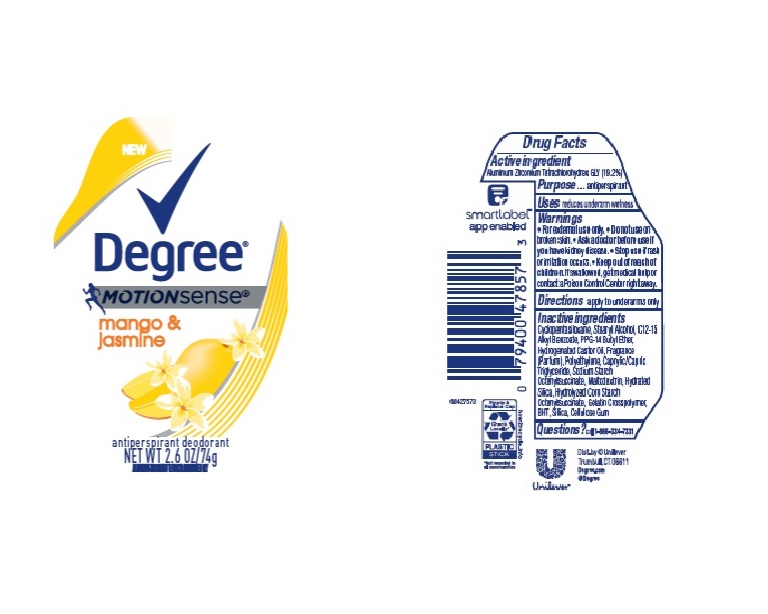 DRUG LABEL: Degree
NDC: 64942-1788 | Form: STICK
Manufacturer: Conopco Inc. d/b/a/ Unilever
Category: otc | Type: HUMAN OTC DRUG LABEL
Date: 20241110

ACTIVE INGREDIENTS: ALUMINUM ZIRCONIUM TETRACHLOROHYDREX GLY 19.2 g/100 g
INACTIVE INGREDIENTS: PPG-14 BUTYL ETHER; STEARYL ALCOHOL; MALTODEXTRIN; SILICON DIOXIDE; ALKYL (C12-15) BENZOATE; HIGH DENSITY POLYETHYLENE; MEDIUM-CHAIN TRIGLYCERIDES; CARBOXYMETHYLCELLULOSE SODIUM, UNSPECIFIED FORM; HYDRATED SILICA; CYCLOMETHICONE 5; HYDROGENATED CASTOR OIL; BUTYLATED HYDROXYTOLUENE

Degree Motionsense Mango & Jasmine Antiperspirant Deodorant

DEGREE MOTIONSENSE MANGO & JASMINE ANTIPERSPIRANT DEODORANT - aluminum zirconium tetrachlorohydrex gly

Degree Motionsense Mango & Jasmine Antiperspirant Deodorant

Drug Facts

Active ingredient

Aluminum Zirconium Tetrachlorohydrex GLY (19.2 %)

Purpose

antiperspirant

Uses

reduces underarm wetness

Warnings

• For external use only.
• Do not use on broken skin .
• Ask a doctor before use if you have kidney disease.
• Stop use if rash or irritation occurs.

• Keep out of reach of children.

If swallowed, get medical help or contact a Poison Control Center right away.

Directions

apply to underarms only

Inactive ingredients

Cyclopentasiloxane, Stearyl Alcohol, C12-15 Alkyl Benzoate, PPG-14 Butyl Ether, Hydrogenated Castor Oil, Fragrance (Parfum), Polyethylene, Caprylic/Capric Triglyceride, Sodium Starch Octenylsuccinate, Maltodextrin, Hydrated Silica, Hydrolyzed Corn Starch Octenylsuccinate, Gelatin Crosspolymer, BHT, Silica, Cellulose Gum

Questions?

Call 1-866-334-7331